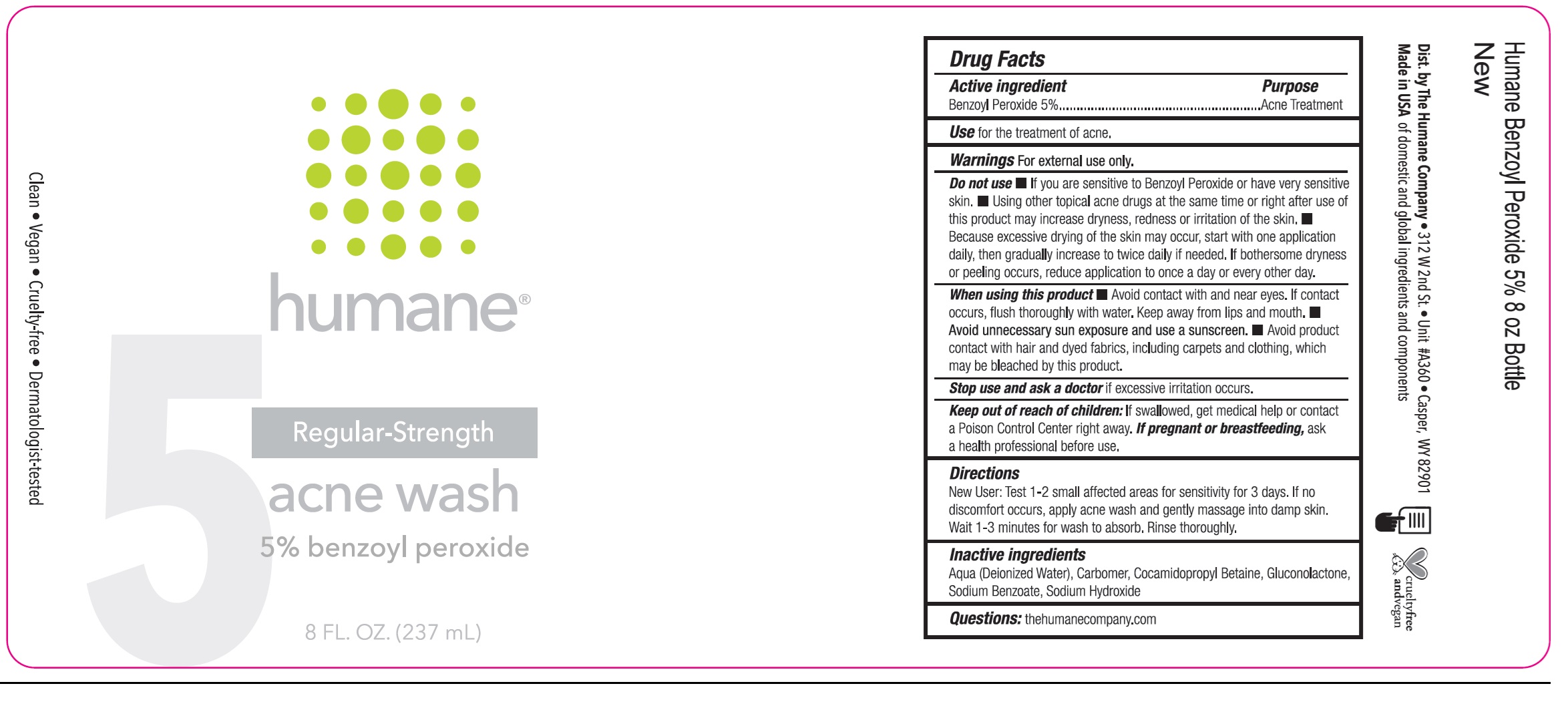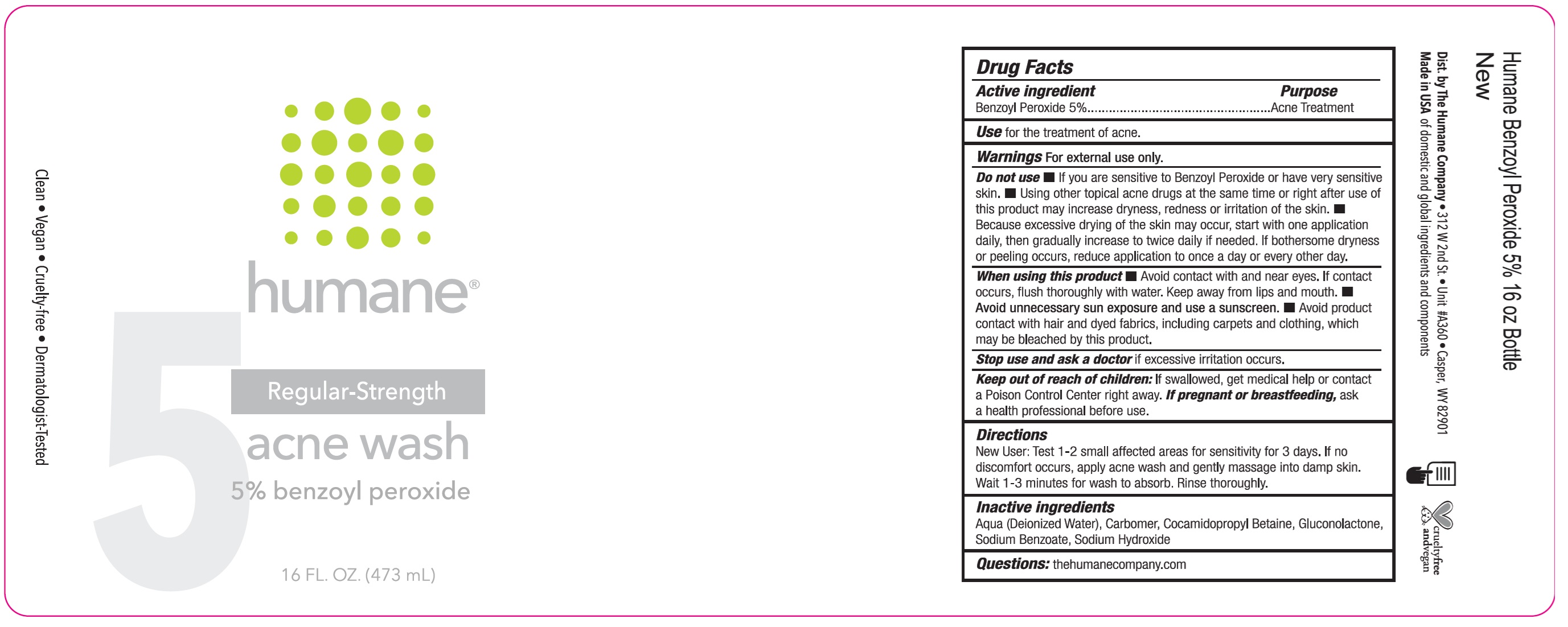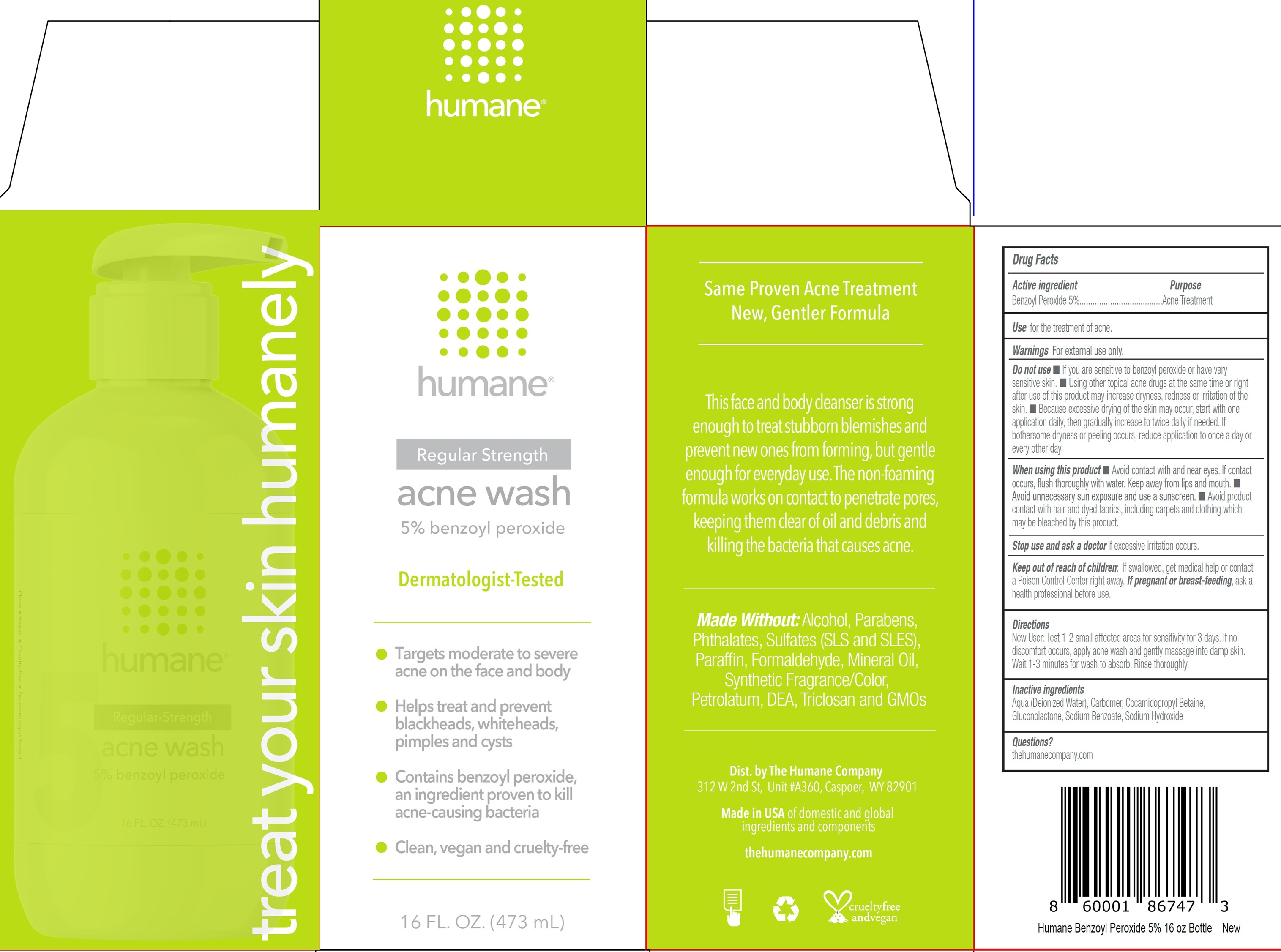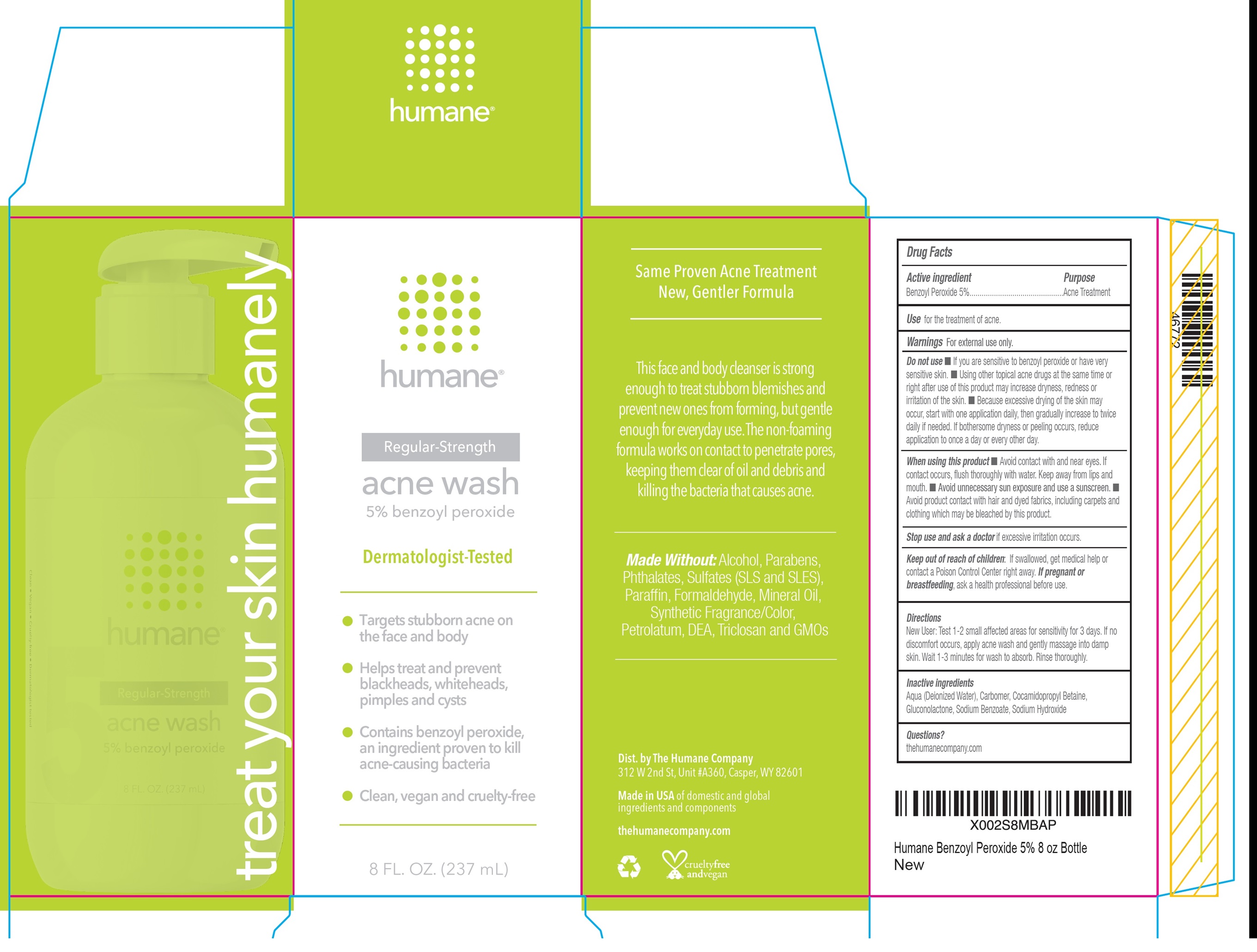 DRUG LABEL: HUMANE Acne Wash 5
NDC: 69919-526 | Form: LIQUID
Manufacturer: Banner 1 LLC
Category: otc | Type: HUMAN OTC DRUG LABEL
Date: 20250924

ACTIVE INGREDIENTS: BENZOYL PEROXIDE 50 mg/1 mL
INACTIVE INGREDIENTS: WATER; CARBOMER HOMOPOLYMER, UNSPECIFIED TYPE; COCAMIDOPROPYL BETAINE; GLUCONOLACTONE; SODIUM BENZOATE; SODIUM HYDROXIDE

HUMANE Acne Wash 5%

Active ingredient

Benzoyl Peroxide 5%

Purpose

Acne Treatment

Use

for the treatment of acne.

Warnings

For external use only.

Do not use

- If you are sensitive to benzoyl peroxide or have very sensitive skin.
- Using other topical acne drugs at the same time or right after use of this product may increase dryness, redness or irritation of the skin.
- Because excessive drying of the skin may occur, start with one application daily, then gradually increase to twice daily if needed. If bothersome dryness or peeling occurs, reduce application to once a day or every other day.

When using this product

- Avoid contact with and near eyes. If contact occurs, flush thoroughly with water. Keep away from lips and mouth.
- Avoid unnecessary sun exposure and use a sunscreen.
- Avoid product contact with hair and dyed fabrics, including carpets and clothing which may be bleached by this product.

Stop use and ask a doctor

if excessive irritation occurs.

Keep out of reach of children:

If swallowed, get medical help or contact a Poison Control Center right away.

If pregnant or breastfeeding,

ask a health professional before use.

Directions

New User: Test 1-2 small affected areas for sensitivity for 3 days. If no discomfort occurs, apply acne wash and gently massage into damp skin. Wait 1-3 minutes for wash to absorb. Rinse thoroughly.

Inactive ingredients

Aqua (Deionized Water), Carbomer, Cocamidopropyl Betaine, Gluconolactone, Sodium Benzoate, Sodium Hydroxide

Questions?

thehumanecompany.com